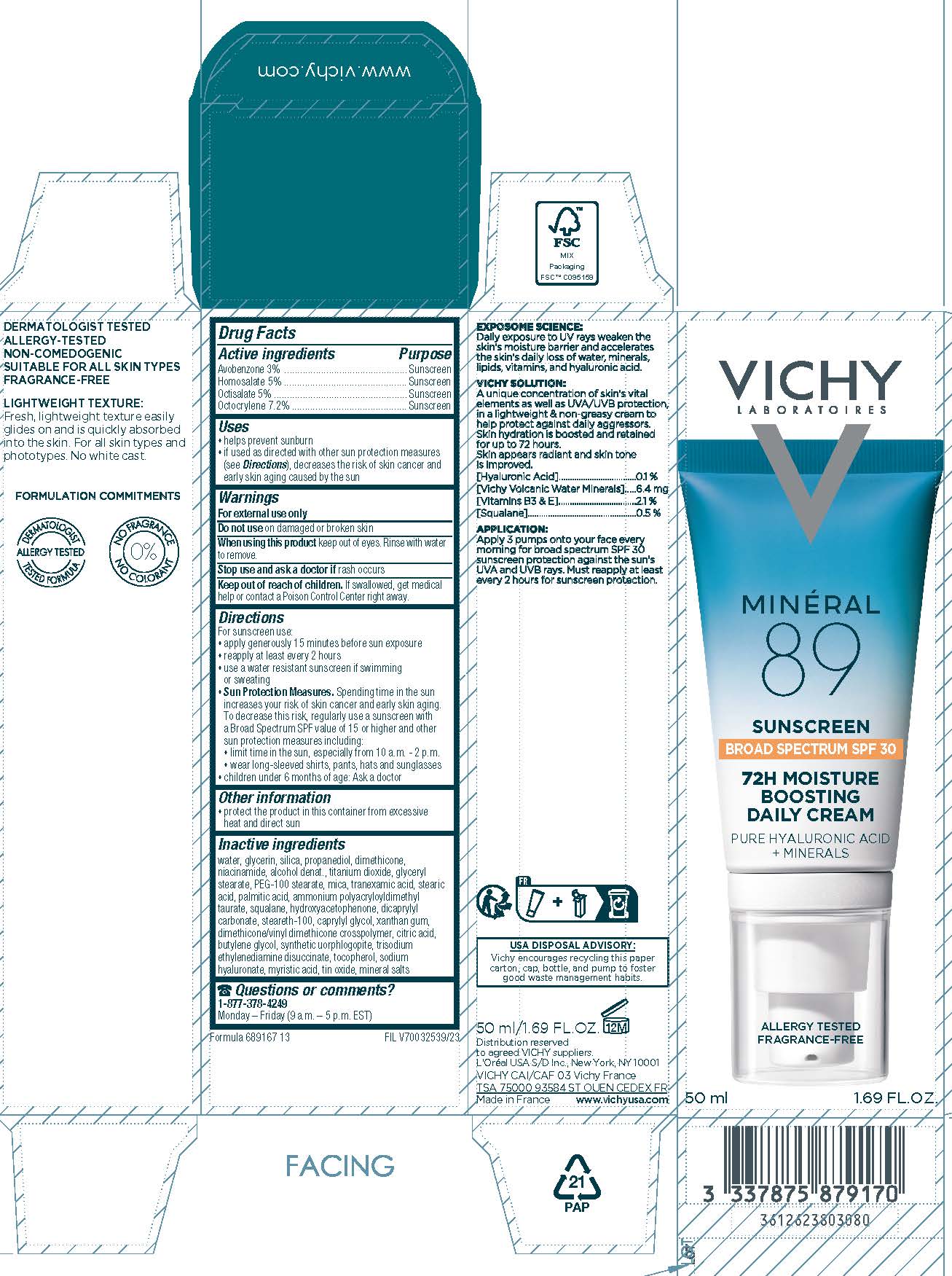 DRUG LABEL: Vichy Laboratoires Mineral 89 Broad Spectrum SPF 30 Sunscreen
NDC: 69625-917 | Form: CREAM
Manufacturer: Cosmetique Active Production
Category: otc | Type: HUMAN OTC DRUG LABEL
Date: 20240714

ACTIVE INGREDIENTS: AVOBENZONE 30 mg/1 mL; HOMOSALATE 50 mg/1 mL; OCTISALATE 50 mg/1 mL; OCTOCRYLENE 72 mg/1 mL
INACTIVE INGREDIENTS: WATER; GLYCERIN; SILICON DIOXIDE; PROPANEDIOL; DIMETHICONE; NIACINAMIDE; ALCOHOL; TITANIUM DIOXIDE; GLYCERYL 1-STEARATE; PEG-100 STEARATE; MICA; TRANEXAMIC ACID; STEARIC ACID; PALMITIC ACID; AMMONIUM POLYACRYLOYLDIMETHYL TAURATE; SQUALANE; HYDROXYACETOPHENONE; DICAPRYLYL CARBONATE; STEARETH-100; CAPRYLYL GLYCOL; XANTHAN GUM; DIMETHICONE/VINYL DIMETHICONE CROSSPOLYMER (HARD PARTICLE); CITRIC ACID MONOHYDRATE; BUTYLENE GLYCOL; MAGNESIUM POTASSIUM ALUMINOSILICATE FLUORIDE; TRISODIUM ETHYLENEDIAMINE DISUCCINATE; TOCOPHEROL; HYALURONATE SODIUM; MYRISTIC ACID; STANNIC OXIDE

Drug Facts

Active ingredients

Avobenzone 3%

Homosalate 5%

Octisalate 5%

Octocrylene 7.2%

Purpose

Sunscreen

Uses

- helps prevent sunburn
- if used as directed with other sun protection measures (see Directions), decreases the risk of skin cancer and early skin aging caused by the sun

Warnings

For external use only

Do not use

on damaged or broken skin

When using this product

keep out of eyes. Rinse with water to remove.

Stop use and ask a doctor if

rash occurs

Keep out of reach of children.

If swallowed, get medical help or contact a Poison Control Center right away.

Directions

For sunscreen use:

- shake well before use

● apply liberally 15 minutes before sun exposure

● reapply:

● after 80 minutes of swimming or sweating

● immediately after towel drying

● at least every 2 hours

● Sun Protection Measures. Spending time in the sun increases your risk of skin cancer and early skin aging. To decrease this risk, regularly use a sunscreen with a Broad Spectrum SPF value of 15 or higher and other sun protection measures including:

● limit time in the sun, especially from 10 a.m. – 2 p.m.

● wear long-sleeved shirts, pants, hats, and sunglasses

● children under 6 months of age: Ask a doctor

Other information

- protect the product in this container from excessive heat and direct sun
- store at 68 – 77° F (20 – 25°C)

Inactive ingredients

water, glycerin, silica, propanediol, dimethicone, niacinamide, alcohol denat., titanium dioxide, glyceryl stearate, PEG-100 stearate, mica, tranexamic acid, stearic acid, palmitic acid,ammonium polyacryloyldimethyl taurate, squalene, hydroxyacetophenone, dicaprylyl carbonate, steareth-100, caprylyl glycol, xanthan gum, dimethicone/vinyl dimethicone crosspolymer, citric acid, butylene glycol, synthetic fluorphlogopite, trisodium ethylenediamine disuccinate, tocopherol, sodium hyaluronate, myristic acid, tin oxide, mineral salts

Questions or comments?

Call toll free 1-877-378-4249

Monday - Friday (9 a.m. to 5 p.m. EST)